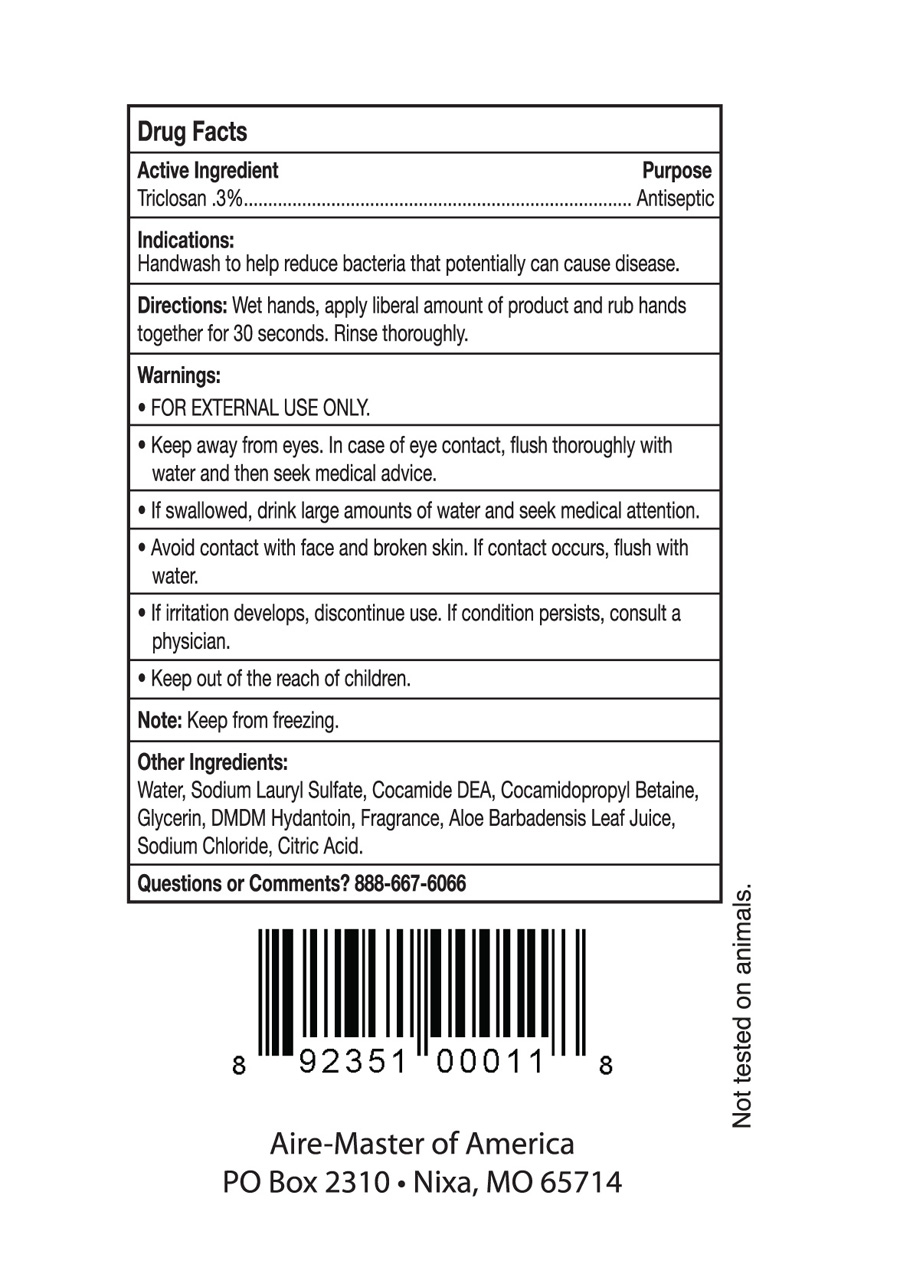 DRUG LABEL: Aire-Master
NDC: 65133-180 | Form: LIQUID
Manufacturer: Aire-Master of America, Inc.
Category: otc | Type: HUMAN OTC DRUG LABEL
Date: 20200129

ACTIVE INGREDIENTS: TRICLOSAN 0.3 g/10 mL
INACTIVE INGREDIENTS: WATER; SODIUM LAURYL SULFATE; COCO DIETHANOLAMIDE; COCAMIDOPROPYL BETAINE; GLYCERIN; DMDM HYDANTOIN; ALOE VERA LEAF; SODIUM CHLORIDE; CITRIC ACID MONOHYDRATE

Active Ingredient

Triclosan .3%

Purpose

Antiseptic

Indications

Handwash to help reduce bacteria that potentially can cause disease.

Directions

Directions: Wet hands, apply leberal amount of product and rub hands

together for 30 seconds. Rinse thoroughly.

Warnings

-FOR EXTERNAL USE ONLY

-Keep away from eyes. In case of eye contact, flush thoroughly with water

and then seek medical advice.

-If swallowed, drink large amounts of water and seek medical attention.

-Avoid contact with face and broken skin. If contact occurs, flush with

water.

-If irritation develops, discontinue use. If condition persists, consult a

doctor.

Keep out of reach of children.

STORAGE AND HANDLING

Note: Keep from freezing.

Other Ingredients

Water, Sodium Lauryl Sulfate, Cocamide DEA, Cocamidopropyl Betaine,

Glycerin, DMDM Hydantoin, Fragrance, Aloe Barbadensis Leaf Juice,

Sodium Chloride, Citric Acid.

Questions or Comments? 888-667-6066